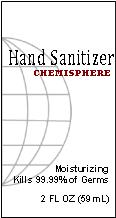 DRUG LABEL: Chemisphere Hand Sanitizer
NDC: 61034-001 | Form: GEL
Manufacturer: Chemisphere Corp
Category: otc | Type: HUMAN OTC DRUG LABEL
Date: 20160509

ACTIVE INGREDIENTS: ALCOHOL 63 mL/100 mL
INACTIVE INGREDIENTS: DIISOPROPYLAMINE; CARBOMER INTERPOLYMER TYPE A (55000 CPS); TERT-BUTYL ALCOHOL; DENATONIUM BENZOATE; GLYCERIN; WATER; ALPHA-TOCOPHEROL ACETATE

ACTIVE INGREDIENT

Ethyl Alcohol 63%

PURPOSE

Antimicrobial

Directions

Wet hands with enough product to cover hands. Rub hands together and allow to dry.

Children under 6 require adult supervision.

Warnings

For external use only.

Flammable. Keep away from heat and flame.

When using this product keep out of eyes. In case of contact with eyes, flush thoroughly with water. Avoid contact with broken skin. Do not inhale or ingest.

Stop use and ask a doctor is irritation or rash develops.

INACTIVE INGREDIENT

Water, Glycerin, Tocopheryl Acetate, T-Butyl Alcohol, Carbomer, Fragrance

INDICATIONS AND USAGE

Hand sanitizer to decrease bacterial on the skin.

Keep out of reach of children. If swallowed, get medical help of contact a Poison Control Center right away.